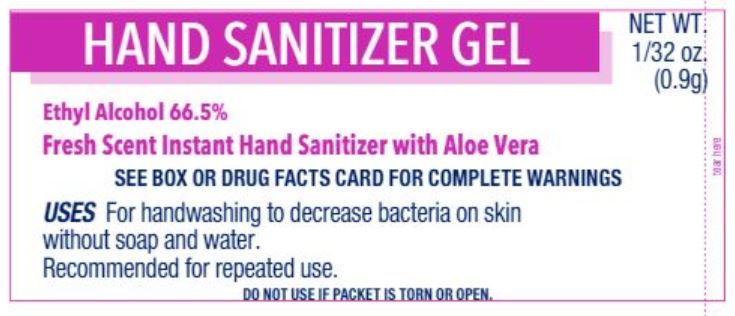 DRUG LABEL: First Aid Direct Hand Sanitizer
NDC: 42961-123 | Form: GEL
Manufacturer: Cintas Corporation
Category: otc | Type: HUMAN OTC DRUG LABEL
Date: 20250924

ACTIVE INGREDIENTS: ALCOHOL 66.5 g/100 g
INACTIVE INGREDIENTS: ALOE; CARBOMER HOMOPOLYMER, UNSPECIFIED TYPE; D&C GREEN NO. 5; D&C YELLOW NO. 10; WATER; TROLAMINE

First Aid Direct Hand Sanitizer

Active ingredient

Ethyl alcohol 66.5%

Purpose

Antiseptic

Uses

- for handwashing to decrease bacteria on skin without soap and water
- recommended for repeated use

Warnings

For external use only.

Flammable, keep away from fire or flame.

Do not use in eyes. If this happens, rinse thoroughly with water.

Stop use and ask a doctor if irritation and redness develop and persists for more than 72 hours

Keep out of reach of children

If ingested get medical help or contact a Poison Control Center right away

Directions

- wet hands & wrists thoroughly with product and allow to dry without wiping
- children under 6 years of age should be supervised while using this product

Inactive ingredients

aloe vera, carbomer, D&C green #5, D&C yellow #10, fragrance, purified water, triethanolamine

Questions or comments?

1-800-327-2704 M-F 8 am - 5 pm

Principal Display Panel

HAND SANITIZER GEL

Ethyl Alcohol 66.5%

Fresh Scent Instant Hand Sanitizer with Aloe Vera

SEE BOX OR DRUG FACTS CARD FOR COMPLETE WARNINGS

USES For hand washing to decrease bateria on skin without soap and water. Recommended for repeated use.

DO NOT USE IF PACKET IS TORN OR OPEN.

NET WT. 1/32 oz. (0.9g)

TEAR HERE